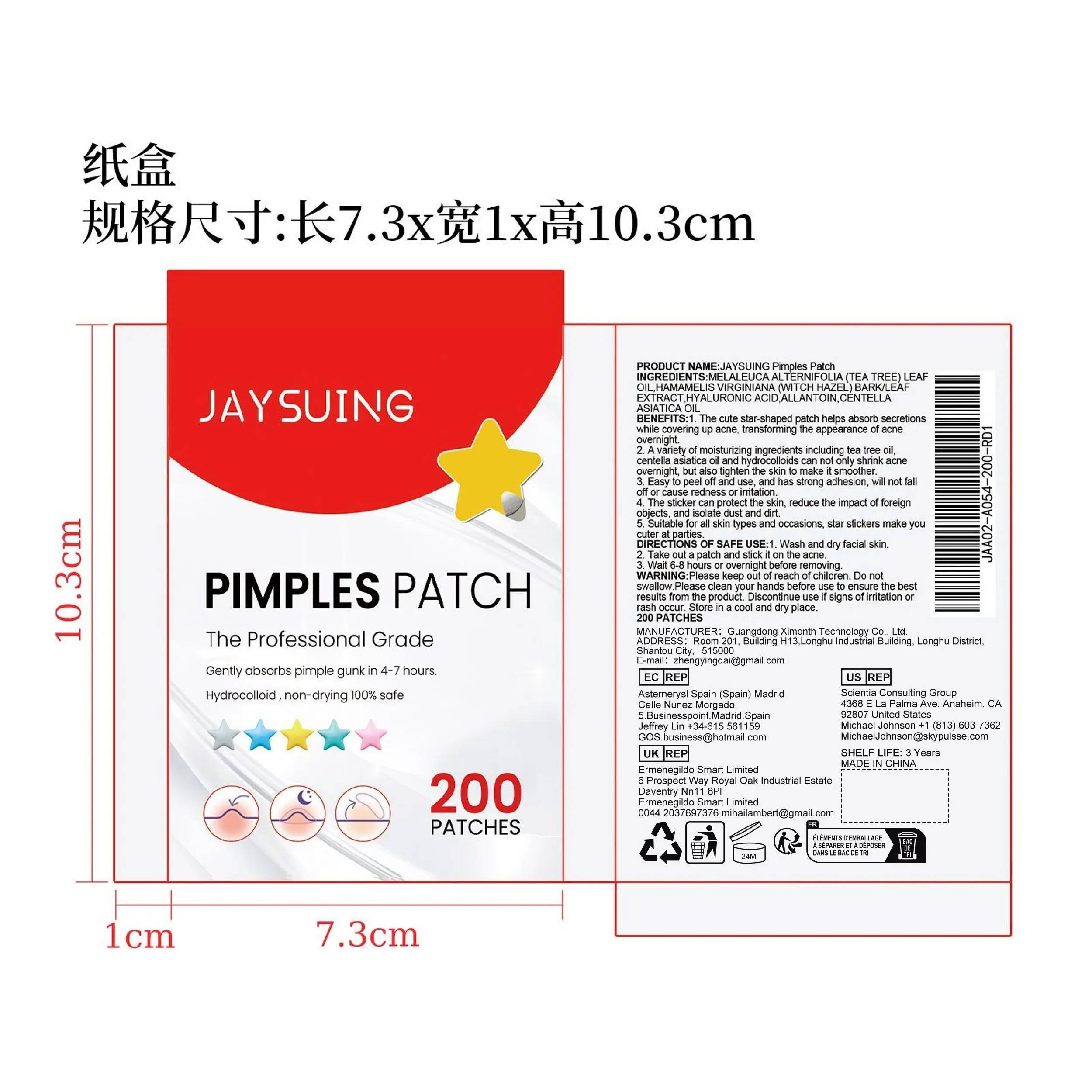 DRUG LABEL: JAYSUING Pimples Patch
NDC: 84660-025 | Form: PATCH
Manufacturer: Guangdong Ximonth Technology Co., Ltd.
Category: otc | Type: HUMAN OTC DRUG LABEL
Date: 20240925

ACTIVE INGREDIENTS: HYALURONIC ACID 1.875 g/12.5 g; HAMAMELIS VIRGINIANA TOP 2.5 g/12.5 g; CENTELLA ASIATICA WHOLE 1.25 g/12.5 g
INACTIVE INGREDIENTS: ALLANTOIN 3.75 g/12.5 g; TEA TREE OIL 3.125 g/12.5 g

Active Ingredient(s)

MELALEUCA ALTERNIFOLIA (TEA TREE) LEAF OIL、HAMAMELIS VIRGINIANA (WITCH HAZEL) BARK/LEAF EXTRACT、HYALURONIC ACID、CENTELLA ASIATICA OIL

Purpose

The cute star-shaped patch helps absorb secretions while covering up acne, transforming the appearance of acne overnight.

Use

1. Wash and dry facial skin.
2. Take out a patch and stick it on the acne.
3. Wait 6-8 hours or overnight before removing.

Warnings

Please keep out of reach of children.Do not swallow.Please clean your hands before use to ensure the best results from the product.Discontinue use if signs of irritation or rash occur.Store in a cool and dry place.

Do not use

Discontinue use if signs of irritation or rash occur

STOP USE

Discontinue use if signs of irritation or rash occur

KEEP OUT OF REACH OF CHILDREN

Please keep out of reach of children. Do not swallow

STORAGE AND HANDLING

Avoid freezing and excessive heat above 40C (104F) ）
Store in a cool and dry place.

INACTIVE INGREDIENT

ALLANTOIN